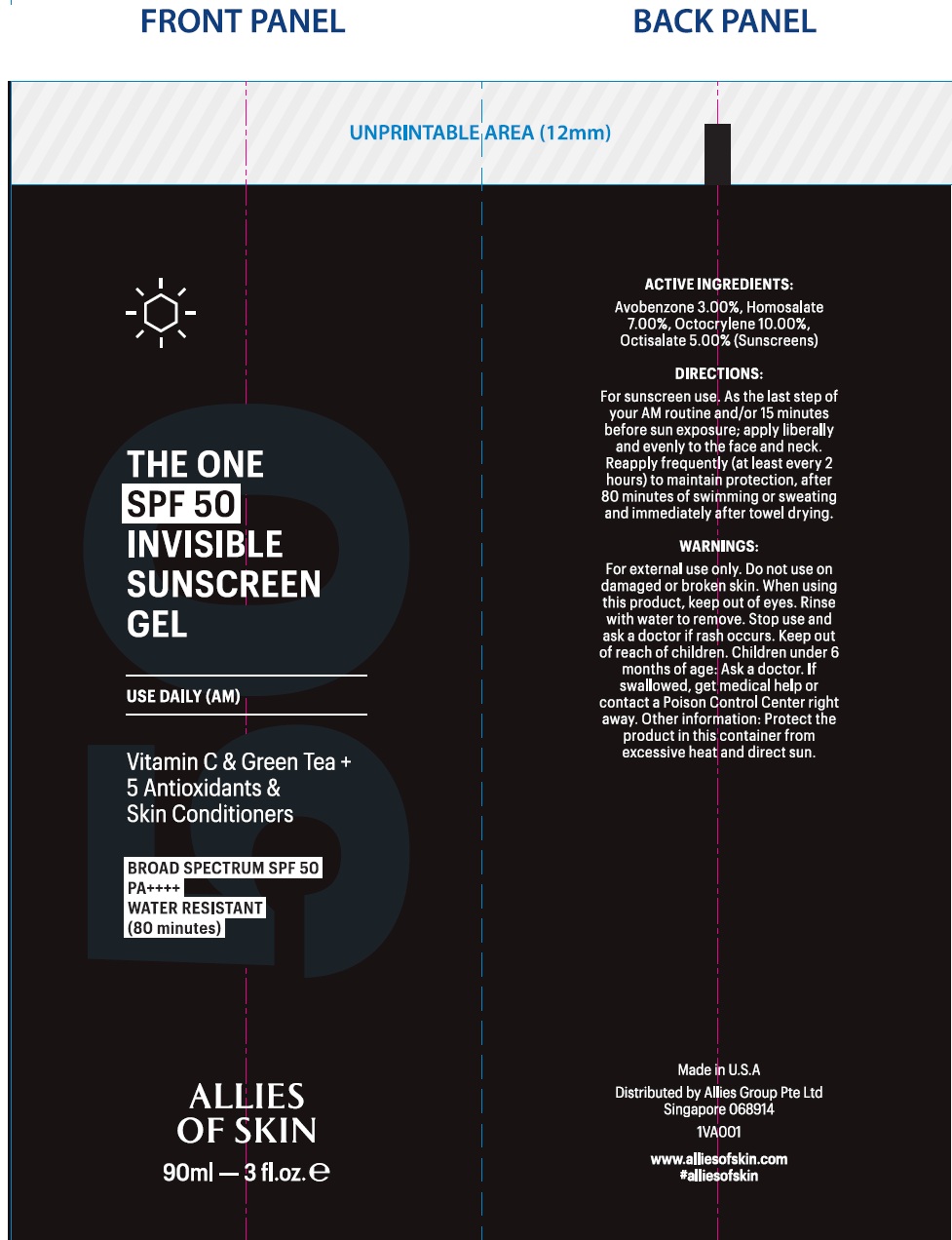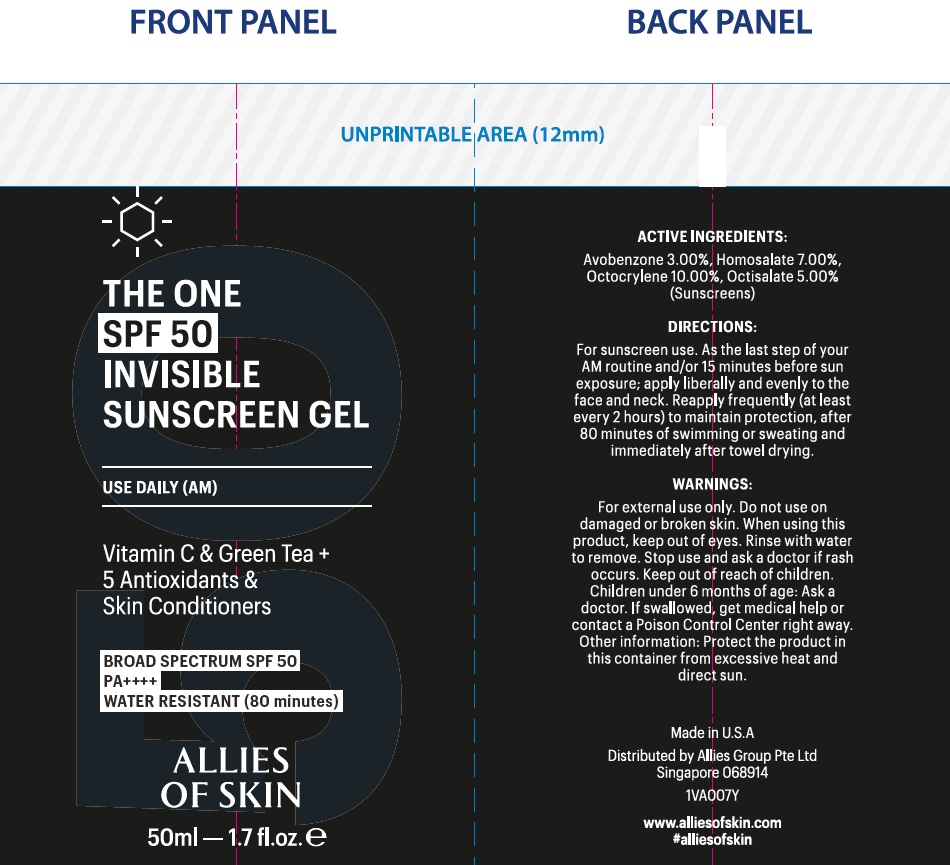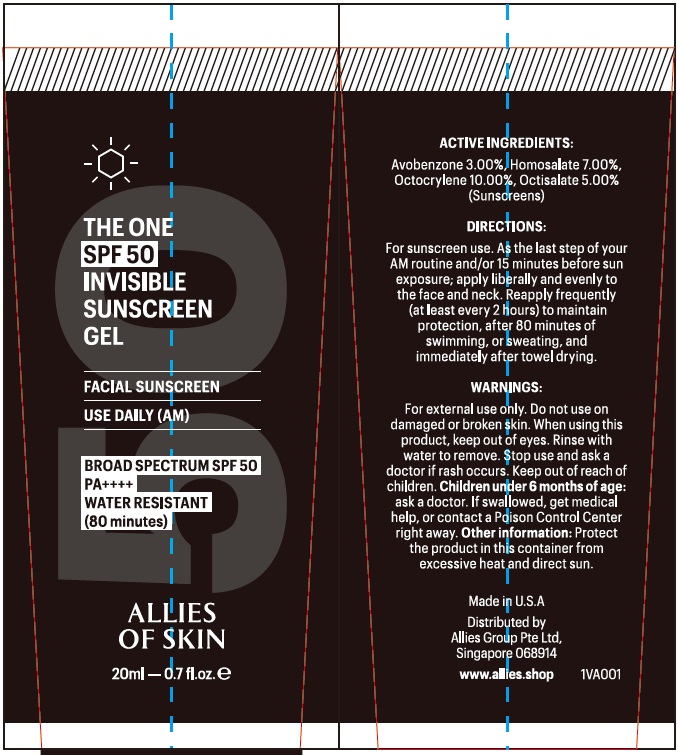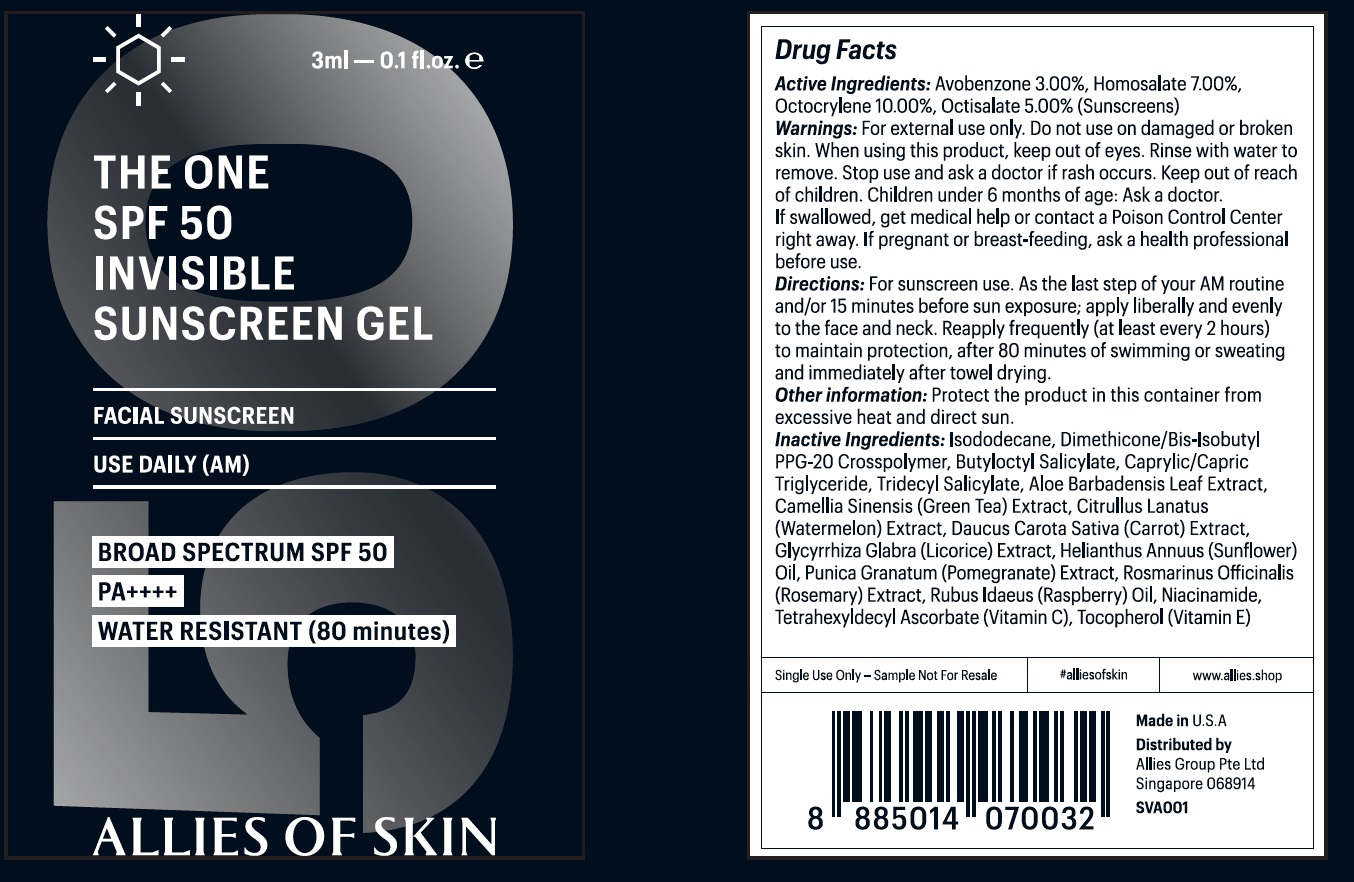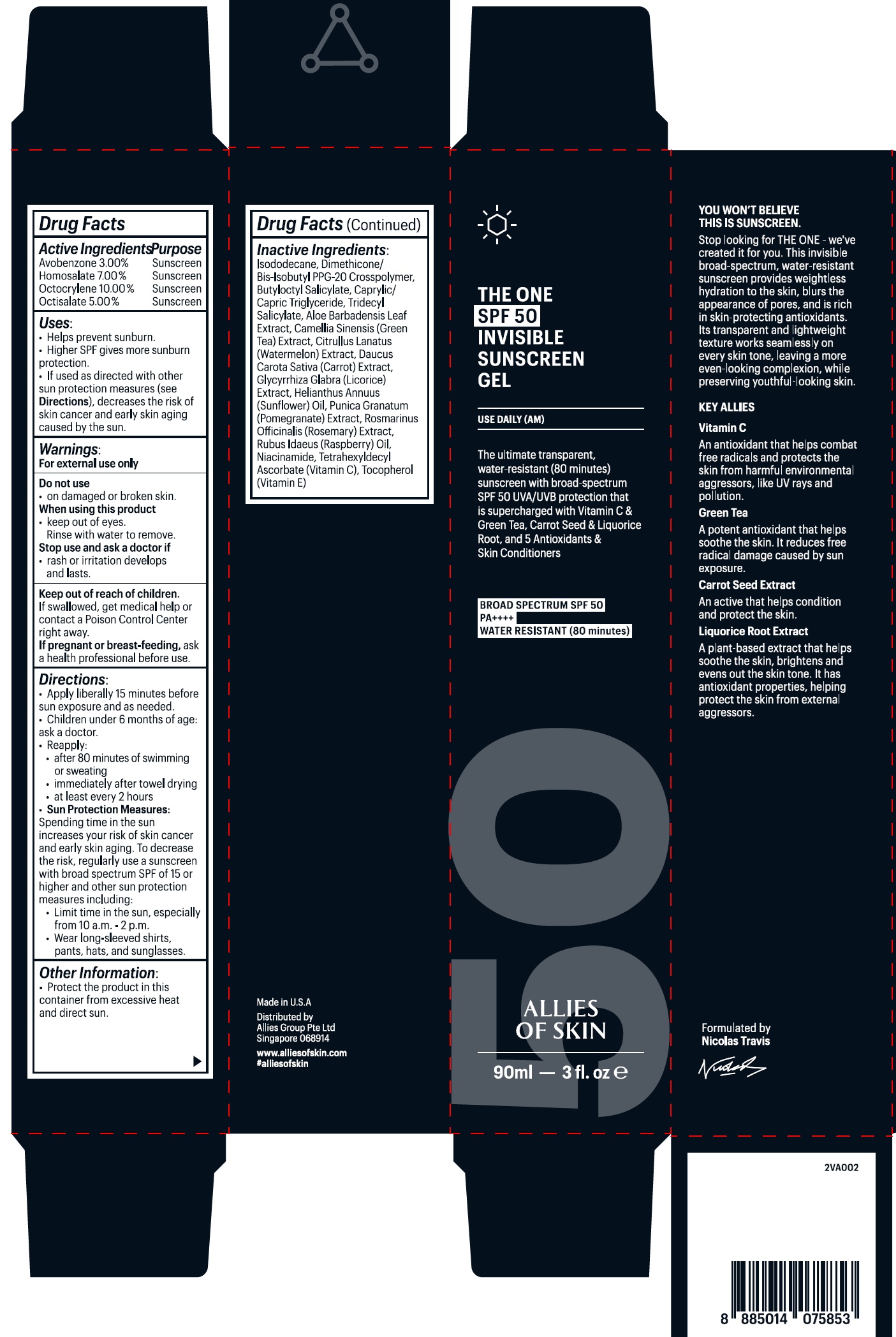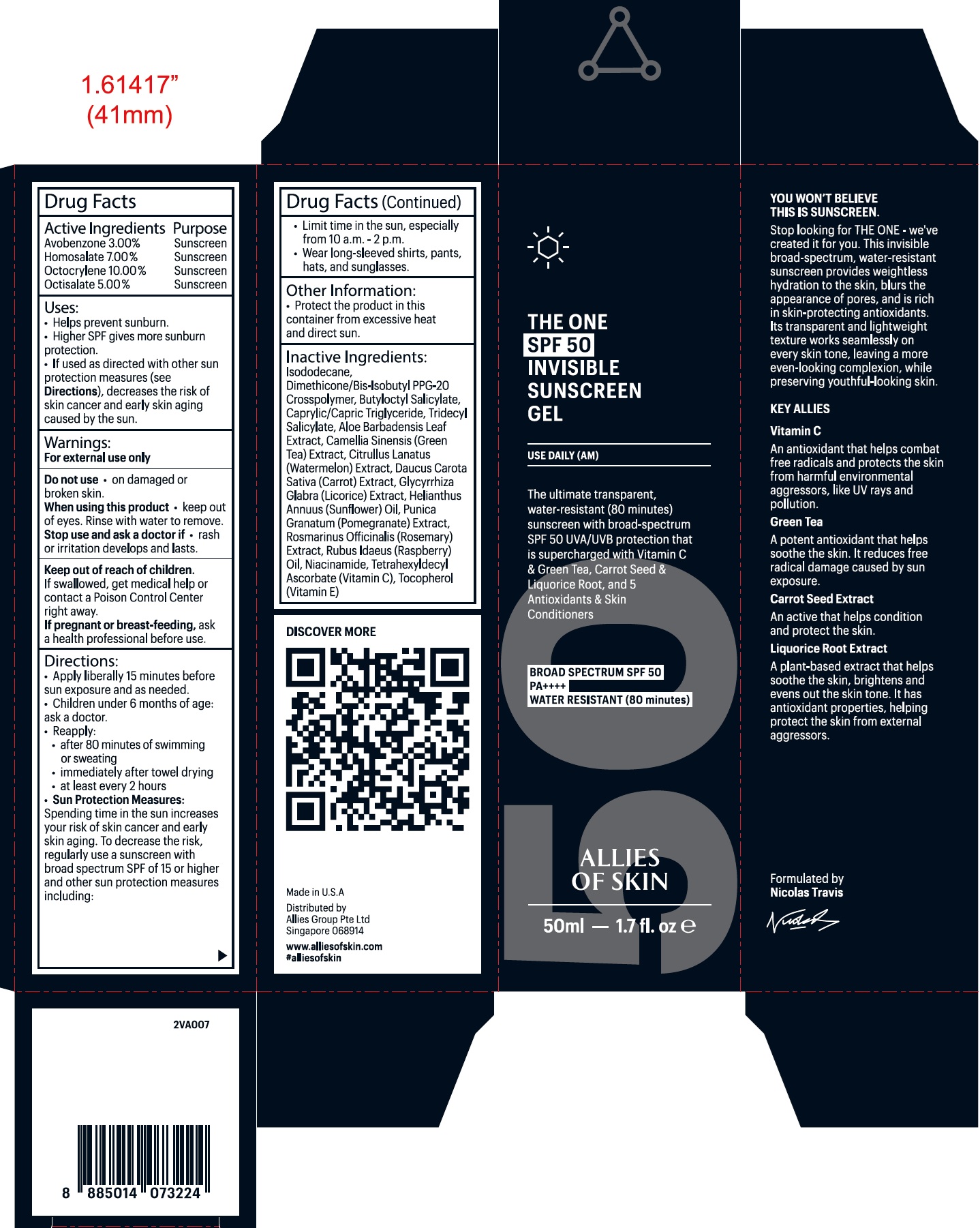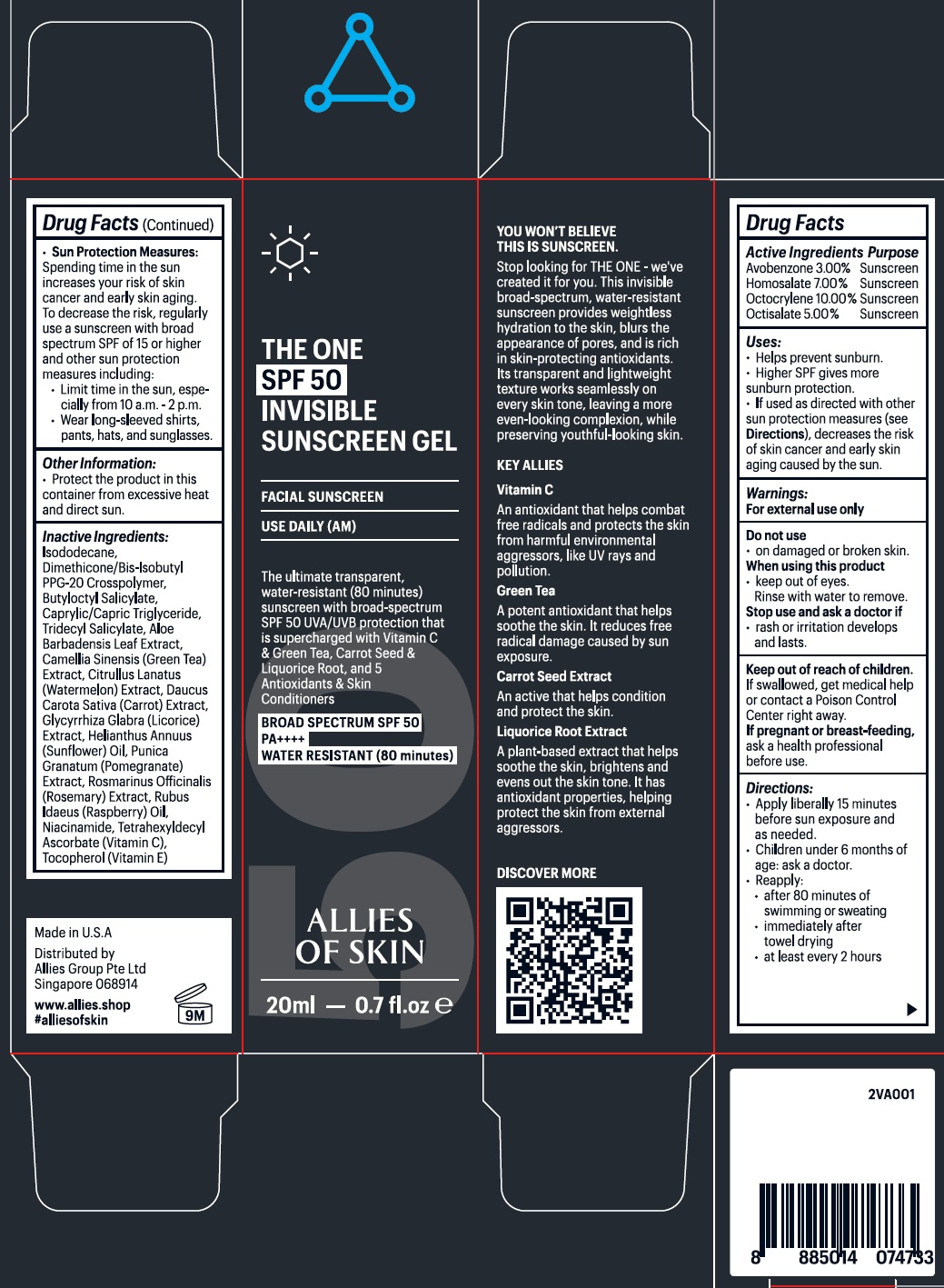 DRUG LABEL: ALLIES OF SKIN The One SPF-50 Invisible Sunscreen
NDC: 83852-438 | Form: GEL
Manufacturer: ALLIES GROUP PTE. LTD.
Category: otc | Type: HUMAN OTC DRUG LABEL
Date: 20250609

ACTIVE INGREDIENTS: AVOBENZONE 30 mg/1 mL; HOMOSALATE 70 mg/1 mL; OCTOCRYLENE 100 mg/1 mL; OCTISALATE 50 mg/1 mL
INACTIVE INGREDIENTS: ISODODECANE; DIMETHICONE/BIS-ISOBUTYL PPG-20 CROSSPOLYMER; BUTYLOCTYL SALICYLATE; MEDIUM-CHAIN TRIGLYCERIDES; TRIDECYL SALICYLATE; ALOE VERA LEAF; GREEN TEA LEAF; WATERMELON; CARROT; GLYCYRRHIZA GLABRA; HELIANTHUS ANNUUS FLOWERING TOP; PUNICA GRANATUM ROOT BARK; ROSEMARY; NIACINAMIDE; TETRAHEXYLDECYL ASCORBATE; TOCOPHEROL

ALLIES OF SKIN: The One SPF-50 Invisible Sunscreen Gel

Active Ingredients

Avobenzone 3.00%,

Homosalate 7.00%,

Octocrylene 10.00%,

Octisalate 5.00%

Purpose

Sunscreen

Uses:

• Helps prevent sunburn. • Higher SPF gives sunburn protection. • If used as directed with other sun protection measures (see

Directions)

, decreases the risk of skin cancer and early skin aging caused by the sun.

Warnings:

For external use only.

Do not use

• on damaged or broken skin.

When using this product

• keep out of eyes. Rinse with water to remove.

Stop use and ask a doctor if

• rash or irritation develops and lasts.

Keep out of reach of children.

If swallowed, get medical help or contact a Poison Control Center right away.

If pregnant or breast-feeding,

ask a health professional before use.

Directions:

• Apply liberally 15 minutes before sun exposure and as needed. • children under 6 months of age: ask a doctor.Reapply:• after 80 minutes of swimming or sweating • immediately after towel drying • at least every 2 hours

• Sun Protection Measures:

Spending time in the sun increases your risk of skin cancer and early skin aging. To decrease this risk, regularly use a sunscreen with broad spectrum SPF of 15 or higher and other sun protection measures including: • Limit time in the sun, especially from 10 a.m. – 2 p.m. • Wear long-sleeved shirts, pants, hats and sunglasses.

Other Information:

• Protect this product in this container from excessive heat and direct sun.

Inactive Ingredients:

Isododecane, Dimethicone/bis-lsobutyl PPG-20 Crosspolymer, Butyloctyl Salicylate, Caprylic/Capric Triglyceride, Tridecyl Salicylate, Aloe Barbadensis Leaf Extract, Camellia Sinensis (Green Tea) Extract, Citrullus Lanatus (Watermelon) Extract, Daucus Carota Sativa (Carrot) Extract, Glycyrrhiza Glabra (Licorice) Extract, Helianthus Annuus (Sunflower) Oil, Punica Granatum (Pomegranate) Extract, Rosmarinus Officinalis (Rosemary) Extract, Rubus Idaeus (Raspberry) Oil, Niacinamide, Tetrahexyldecyl Ascorbate (Vitamin C), Tocopherol (Vitamin E)